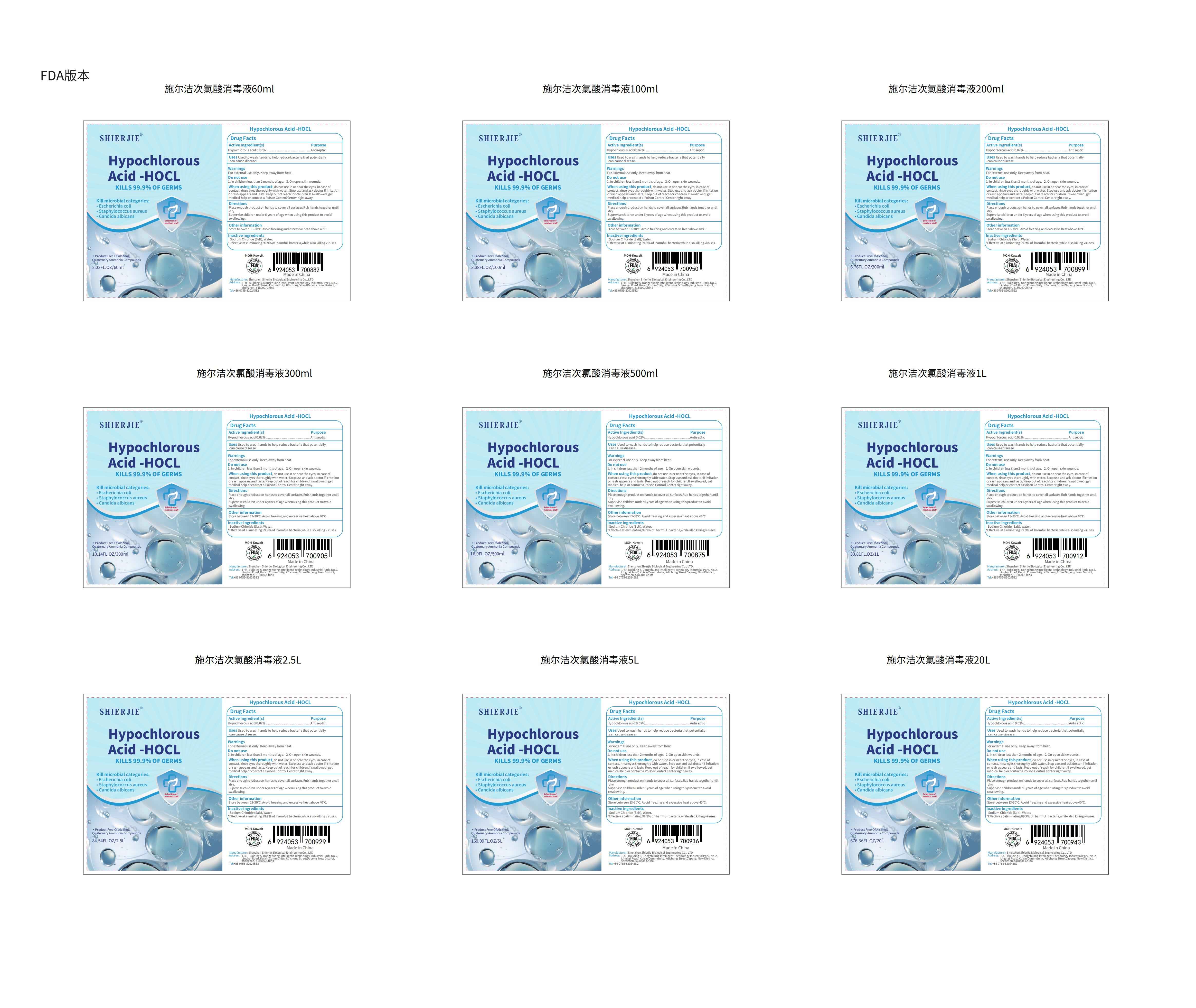 DRUG LABEL: Shierjie Hypochlorous Acid
NDC: 43116-032 | Form: LIQUID
Manufacturer: Shenzhen Shierjie Biological Engineering Co., LTD
Category: otc | Type: HUMAN OTC DRUG LABEL
Date: 20231120

ACTIVE INGREDIENTS: HYPOCHLOROUS ACID 0.02 g/100 mL
INACTIVE INGREDIENTS: WATER; SODIUM CHLORIDE

Active Ingredient

Hypochlorous acid 0.02%

Purpose

Antiseptic, antiseptic

Use

Used to wash hands to help reduce bacteria that potentiallycancause disease

Warnings

For external use only. Keep away from heat

Do not use

1.In children less than 2 months ofage.

2. On open skin wounds

When Using

do not use in ornear the eyes,in case ofcontact, rinse eyes thoroughly with water.

Stop Use

Stop use and ask doctor if irritationor rash appears and lasts. Keep out of reach for children.lf swallowed, getmedical help or contact a Poison Control Center right away.

Ask Doctor

ask doctor if irritationor rash appears and lasts. Keep out of reach for children.lf swallowed, getmedical help or contact a Poison Control Center right away.

Keep Oot Of Reach Of Children

Supervise children under 6 years of age when usingthis productto avoid
swallowing.

Directions

Place enough product on hands to cover all surfaces.Rub hands together unti dry.Supervise children under 6 years of age when usingthis productto avoid
swallowing.

Other information

Store between 13-30°C. Avoid freezing and excessive heat above 40°C.

Inactive ingredients

Sodium Chloride (Salt), Water